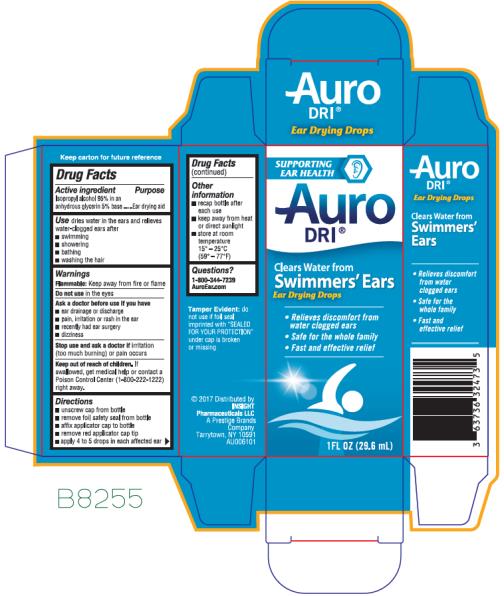 DRUG LABEL: Auro Dri
NDC: 63736-327 | Form: LIQUID
Manufacturer: Insight Pharmaceuticals LLC
Category: otc | Type: HUMAN OTC DRUG LABEL
Date: 20241025

ACTIVE INGREDIENTS: ISOPROPYL ALCOHOL 95 mL/100 mL
INACTIVE INGREDIENTS: GLYCERIN

Auro Dri

AURO-DRI ®

Drug Facts

Active ingredient

Isopropyl alcohol 95% in an anhydrous glycerin 5% base

Purpose

Ear drying aid

Use

dries water in the ears and relieves water-clogged ears after

- swimming
- showering
- bathing
- washing the hair

Warnings

Flammable

Keep away from fire or flame

Do not use

in the eyes

Ask a doctor before use if you have

- ear drainage or discharge
- pain, irritation or rash in the ear
- had ear surgery
- dizziness

Stop use and ask a doctor if

irritation (too much burning) or pain occurs

Keep out of reach of children.

If swallowed, get medical help or contact a Poison Control Center right away.

Directions

- unscrew cap from bottle
- remove foil safety seal from bottle
- affix applicator cap to bottle
- remove red applicator cap tip
- apply 4 to 5 drops in each affected ear

Other information

- recap bottle after each use
- keep away from heat or direct sunlight
- store at room temperature 15° – 25°C (59° – 77°F)
- do not use if foil seal imprinted with "SEALED FOR YOUR PROTECTION" under cap is broken or missing
- keep carton for full drug facts

Inactive ingredient

glycerin

Questions?

1-800-344-7239 Aurodri.com

PRINCIPAL DISPLAY PANEL

29.6 mL Bottle Carton
AURO- DRI®
ISOPROPYL ALCOHOL 95% in an
ANHYDROUS GLYCERIN 5% base
– Ear Drying Aid
CLEARS WATER FROM
SWIMMERS' EARS
1 FL OZ (29.6 mL)